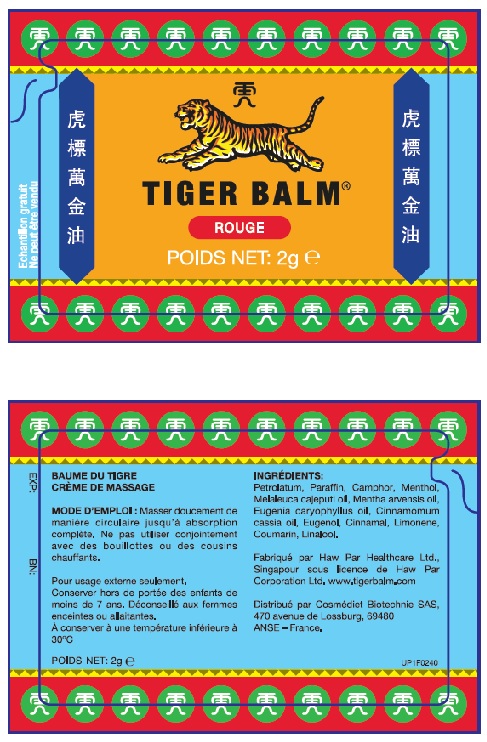 DRUG LABEL: Tiger Balm Red
NDC: 66761-803 | Form: OINTMENT
Manufacturer: Haw Par Healthcare Ltd.
Category: otc | Type: HUMAN OTC DRUG LABEL
Date: 20241230

ACTIVE INGREDIENTS: CAMPHOR (NATURAL) 110 g/1 kg; MENTHOL, UNSPECIFIED FORM 100 g/1 kg
INACTIVE INGREDIENTS: PETROLATUM; PARAFFIN; MELALEUCA CAJUPUTI LEAF OIL; MENTHA ARVENSIS LEAF OIL; CLOVE OIL; CHINESE CINNAMON LEAF OIL; EUGENOL; CINNAMALDEHYDE; LIMONENE, (+)-; COUMARIN; LINALOOL, (+/-)-

TIGER BALM® ROUGE

PRODUCT FOR EXPORT ONLY

Pouch Label

Ultra Strength TIGER BALM®

POIDS NET 2g:

EXP: BN:

res